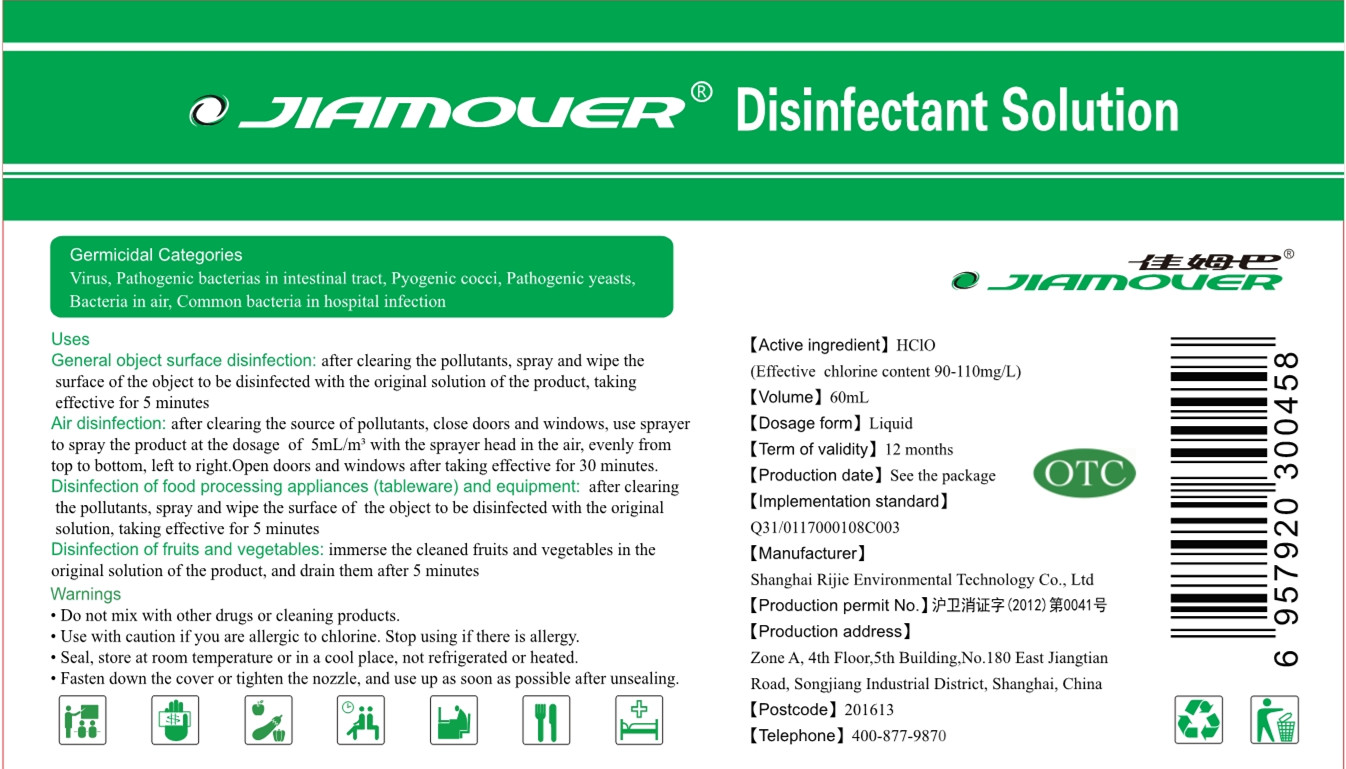 DRUG LABEL: Disinfectant Solution
NDC: 54125-008 | Form: LIQUID
Manufacturer: Shanghai Rijie Environmental Technology Co., Ltd
Category: otc | Type: HUMAN OTC DRUG LABEL
Date: 20200428

ACTIVE INGREDIENTS: HYPOCHLOROUS ACID 0.006 g/60 mL
INACTIVE INGREDIENTS: WATER

DOSAGE AND ADMINISTRATION

Seal, store at room temperature or in a cool place,not refrigerated or heated.

INACTIVE INGREDIENT

purified water

INDICATIONS AND USAGE

after clearing the source of pollutants, close doors and windows, use sprayer to spray the product at the dosage of 5mL/m' with the sprayer head in the air, evenly from top to bottom, lcft to right.Open doors and windows after taking efective for 30 minutes.Disinfection of food processing appliances (tableware) and equipment: after clearing the pollutants, spray and wipe the surface of the object to be disinfected with the original solution, taking effective for 5 minutes

ACTIVE INGREDIENT

hypochlorous acid

keep out of children

PURPOSE

Disinfection
Sterilization

WARNINGS

1.Do not mix with other drugs or cleaning products.
2.Use with caution if you are alergie to chlorine. Stop using if there is allergy.
3.Seal, store at room temperature or in a cool place,not refrigerated or heated.
4.Use up as soon as possible after unsealing.